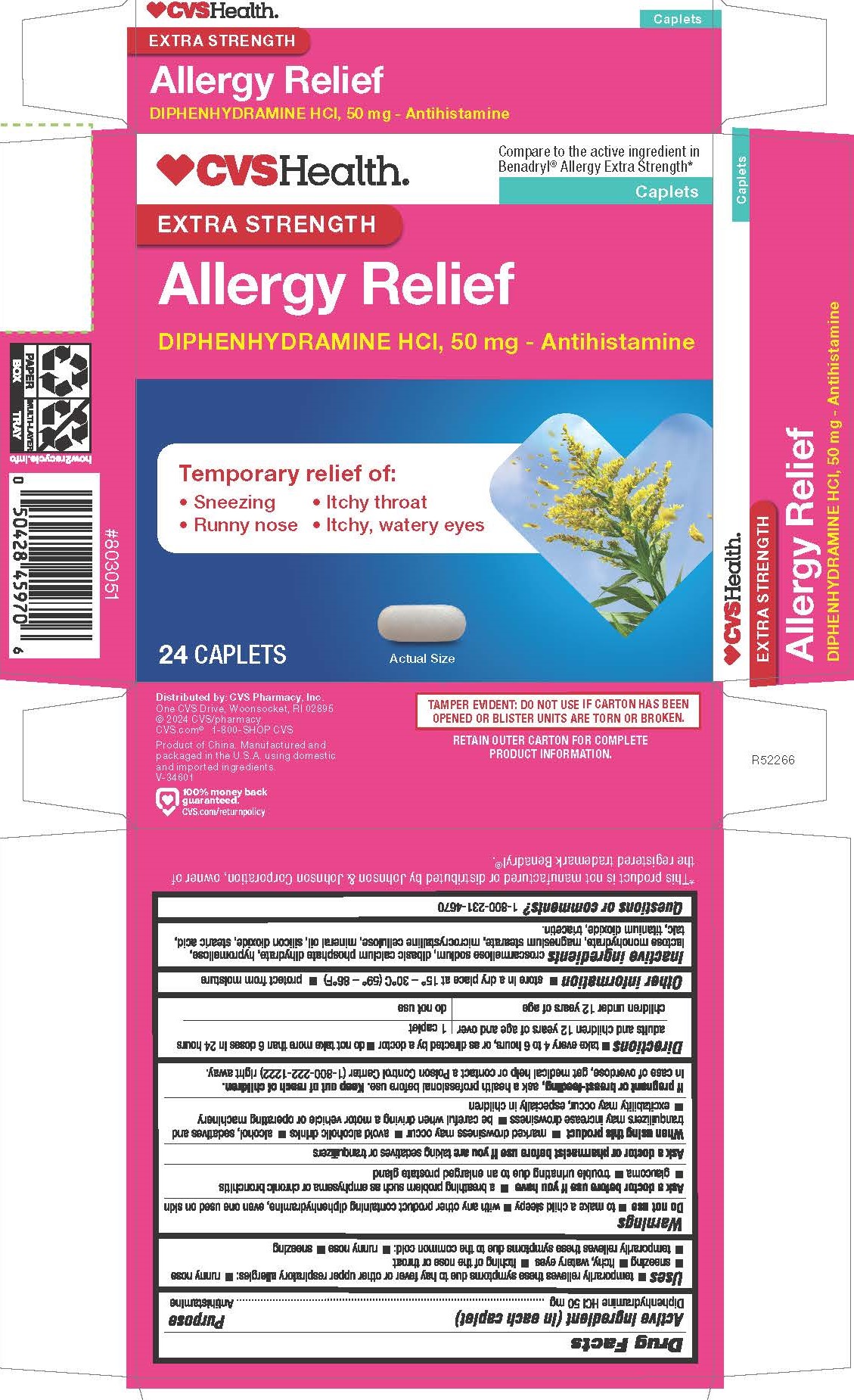 DRUG LABEL: Diphenhydramine HCl
NDC: 51316-221 | Form: TABLET, COATED
Manufacturer: CVS Pharmacy, Inc.
Category: otc | Type: HUMAN OTC DRUG LABEL
Date: 20240201

ACTIVE INGREDIENTS: DIPHENHYDRAMINE HYDROCHLORIDE 50 mg/1 1
INACTIVE INGREDIENTS: CROSCARMELLOSE SODIUM; DIBASIC CALCIUM PHOSPHATE DIHYDRATE; MAGNESIUM STEARATE; SILICON DIOXIDE; TITANIUM DIOXIDE; TRIACETIN; LIGHT MINERAL OIL; TALC; HYPROMELLOSES; LACTOSE MONOHYDRATE; MICROCRYSTALLINE CELLULOSE; STEARIC ACID

0110-CVS

Drug Facts

Active ingredient (in each caplet)

Diphenhydramine HCl 50 mg

Purpose

Antihistamine

Uses

temporarily relives symptoms due to hay fever or other upper respiratory allergies:

- runny nose
- sneezing
- itchy, watery eyes
- itching of the nose or throat

temporarily relives these symptoms due to the common cold:

- runny nose
- sneezing

WARNINGS

Do not use

- to make a child sleepy
- with any other product containing diphenhydramine, even one used on skin

Ask a doctor before use if you have

- a breathing problem such as emphysema or chronic bronchitis
- glaucoma
- trouble urinating due to an enlarged prostate gland

Ask a doctor or pharmacist before use if you are taking sedatives or tranquilizers

When using this product

- marked drowsiness mau occur
- avoid alcoholic drinks
- alcohol, sedatives and tranquilizers may increase drowsiness
- be careful when driving a motor vehicle or operating machinery
- excitability may occur, especially in children

PREGNANCY OR BREAST FEEDING

If pregnant or brest-feeding, ask a health professional before use.

Keep out of reach of children.

OVERDOSAGE

In case of overdose, get medical help or contact a Poison Control Center (1-800-222-1222) right away.

Directions

take every 4 to 6 hours, or as directed by a doctor

do not take more than 6 doses in 24 hours

adults and children 12 years of age and over | 1 caplet
children under 12 years of age | do not use

Other information

- store in a dry place at 15º - 30º C (59º - 86º F).
- ptotect from moisture

INACTIVE INGREDIENT

croscarmellose sodium, dibasic calcium phosphate dihydrate, hypromellose, lactose monohydrate, magnesium stearate, microcrystalline cellulose, mineral oil, silicon dioxide, stearic acid, talc, titanium dioxide, triacetin.

QUESTIONS

1-800-231-4670

Distributed by: CVS Pharmacy, Inc.
One CVS Drive, Woonsocket, RI 02895
© 2024 CVS/pharmacy CVS.com® 1-800-SHOP CVS
Product of China. Manufactured and packaged in the U.S.A. using domestic and imported ingredients.
V-34601

TAMPER EVIDENT: DO NOT USE IF CARTON HAS BEEN OPENED OR BLISTER UNITS ARE TORN OR BROKEN.

RETAIN OUTER CARTON FOR COMPLETE PRODUCT INFORMATION.

* This product is not manufactured or distributed by Johnson & Johnson Corporation, owner of the registered trademark Benadryl®.

PACKAGE LABEL

Compare to the active ingredient in Benadryl® Allergy Extra Strength*

Extra Strength

Allergy Relief

Diphenhydramine HCl, 50mg

Antihistamine

Temporatry relief of

Sneezing

Itchy throat

Runny nose

Itchy, watery eyes

24 Caplets